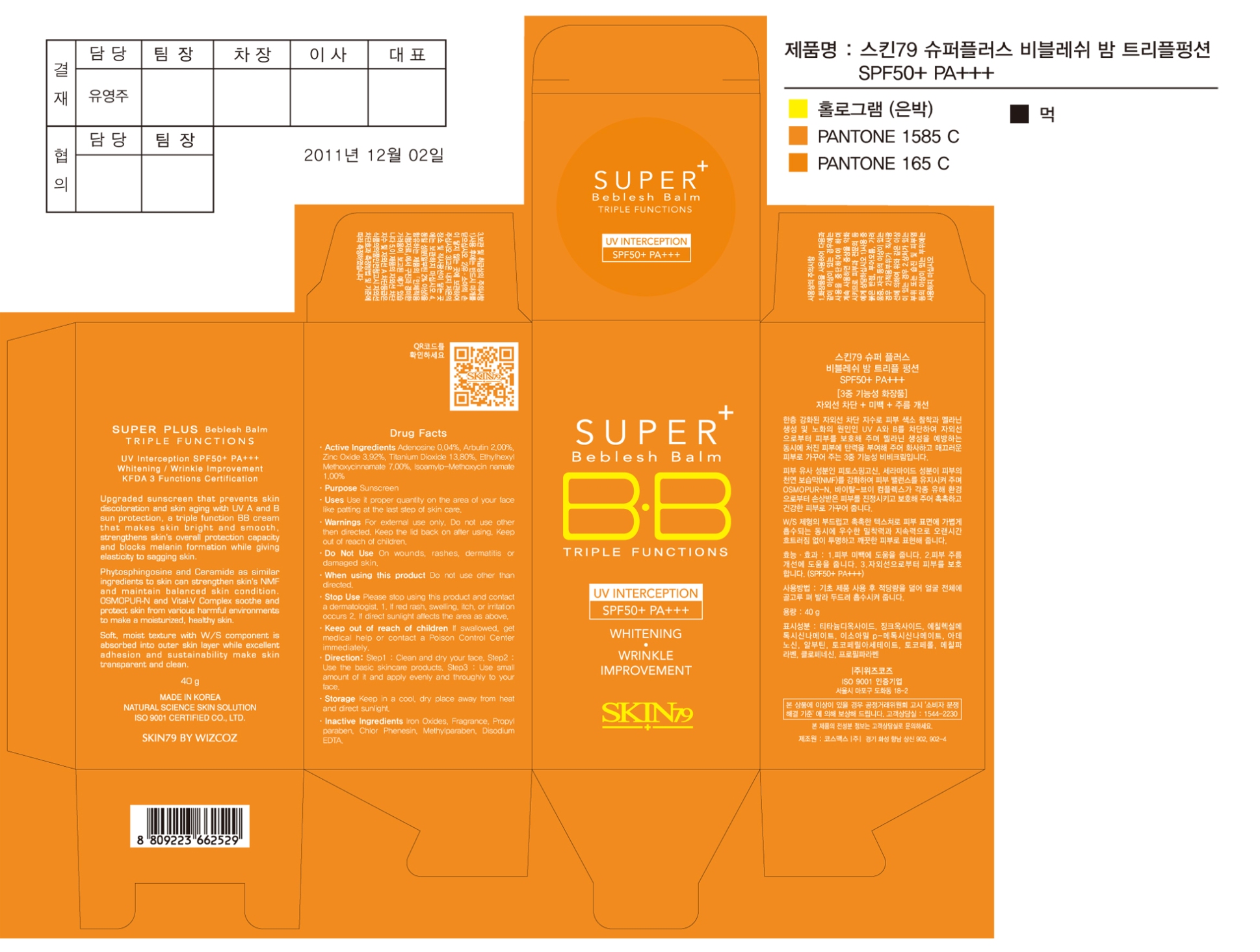 DRUG LABEL: Super Plus Beblesh Balm Triple Functions SPF50 Plus PA 3Plus (40g)
NDC: 49715-007 | Form: CREAM
Manufacturer: WIZCOZ CORPORATION LTD
Category: otc | Type: HUMAN OTC DRUG LABEL
Date: 20111201

ACTIVE INGREDIENTS: TITANIUM DIOXIDE 5.52 g/40 g; ZINC OXIDE 1.569 g/40 g; OCTINOXATE 2.8 g/40 g; AMILOXATE 0.4 g/40 g; ARBUTIN 0.8 g/40 g; ADENOSINE 0.016 g/40 g
INACTIVE INGREDIENTS: BROWN IRON OXIDE; CHLORPHENESIN; DISODIUM EDTA-COPPER; METHYLPARABEN; PROPYLPARABEN

Purpose: Sunscreen

ACTIVE INGREDIENT

Active Ingredients: Adenosine 0.04%, Arbutin 2.00%, Octinoxate 7.00%, Amiloxate 1.00%, Titanium Dioxide 13.80%, Zinc Oxide 3.92%

When using this product: Do not use other than directed

Do Not Use: On wounds, rashes, dermatitis or damaged skin

Keep Out of Reach of Children: If swallowed, get medical help or contact a Poison Control Center immediately

Stop Use: Please stop using this product and contact a dermatologist.
1. If red rash, swelling, itch or irritation occurs
2. If direct sunlight affects the area as above

WARNINGS

Warnings: For external use only. Do not use other than directed. Keep the lid back on after using

STORAGE AND HANDLING

Storage: Keep in a cool, dry place away from heat and direct sunlight

DESCRIPTION

Direction:
Step 1: Clean and dry your face
Step 2: Use the basic skincare products
Step 3: Use small amount of it and apply evenly and thoroughly to your face

INACTIVE INGREDIENT

Inactive Ingredients: Chlorphenesin, Disodium EDTA, Iron Oxide, Methylparaben, Propylparaben